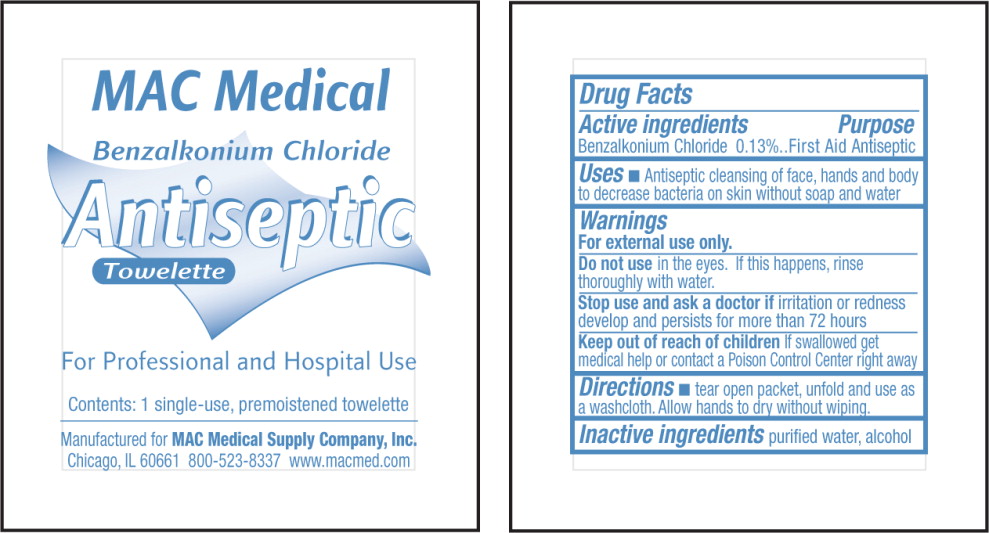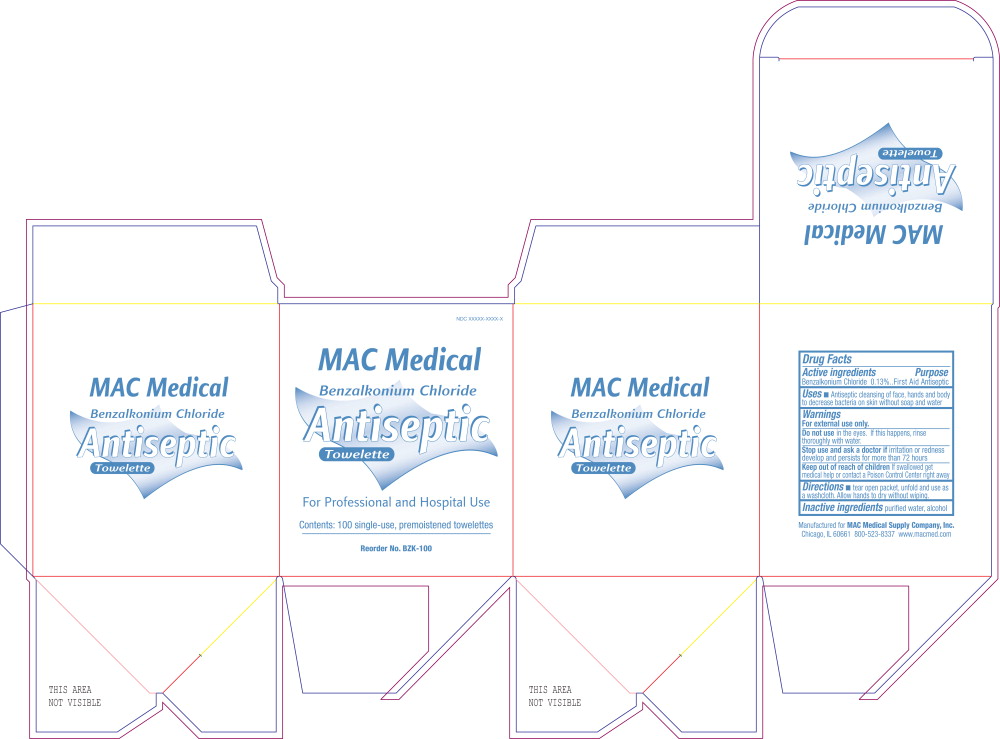 DRUG LABEL: Antiseptic
NDC: 52116-7100 | Form: LIQUID
Manufacturer: MAC Medical Supply Company, Inc.
Category: otc | Type: HUMAN OTC DRUG LABEL
Date: 20130212

ACTIVE INGREDIENTS: benzalkonium chloride 1.2478 g/1 L
INACTIVE INGREDIENTS: alcohol; water

Drug Facts

Active Ingredients

Benzalkonium Chloride 0.13%

Purpose

First Aid Antiseptic

Uses

- Antiseptic cleansing of face, hands and body to decrease bacteria on skin without soap and water

Warnings

For external use only

Do not use in the eyes. If this happens, rinse thoroughly with water.

Stop use and ask doctor if irritation or redness develop and persists for more than 72 hours

Keep out of reach of children If swallowed get medical help or contact a Poison Control Center right away

Directions

- tear open packet, unfold and use as a washcloth. Allow hands to dry without wiping.

Inactive ingredients

purified water, alcohol

PRINCIPAL DISPLAY PANEL – packet label

MAC Medical

Benzalkonium Chloride
Antiseptic
Towelette

For Professional and Hospital Use

Contents: 1 single-use, premoistened towelette

Manufactured for MAC Medical Supply Company, Inc.
Chicago, IL 60661 800-523-8337

PRINCIPAL DISPLAY PANEL – box label

NDC 61010-7110-1

MAC Medical

Benzalkonium Chloride
Antiseptic
Towelette

For Professional and Hospital Use

Contents: 100 single-use, premoistened towelettes

Reorder No. BZK-100